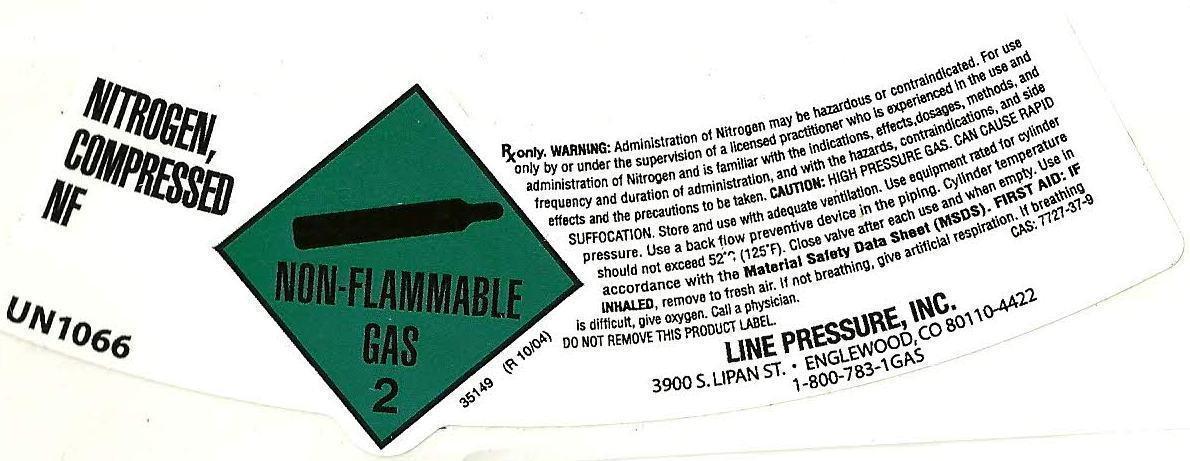 DRUG LABEL: Nitrogen
NDC: 24670-0001 | Form: GAS
Manufacturer: Line Pressure
Category: prescription | Type: HUMAN PRESCRIPTION DRUG LABEL
Date: 20130211

ACTIVE INGREDIENTS: NITROGEN 99 L/100 L

Nitrogen